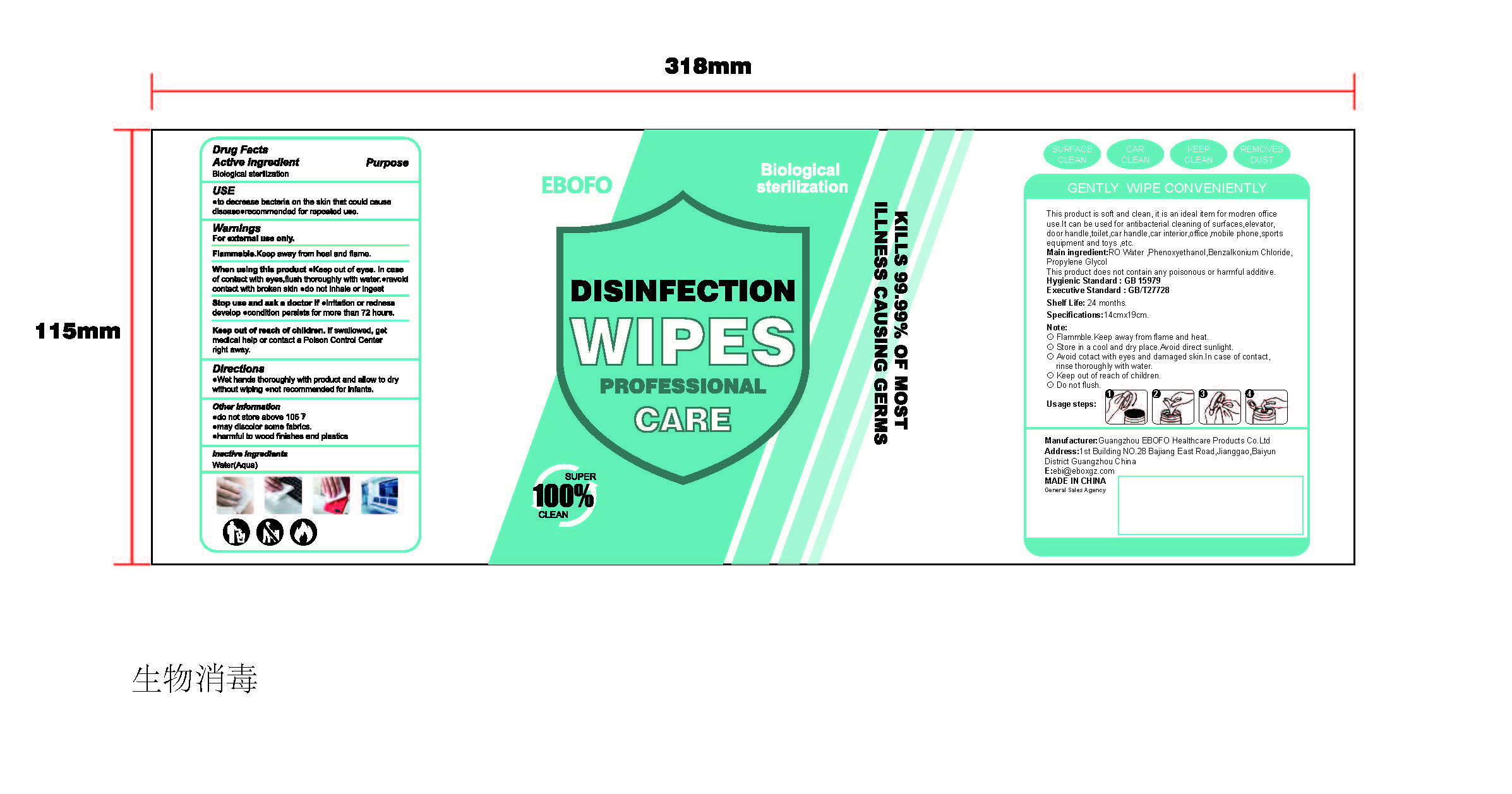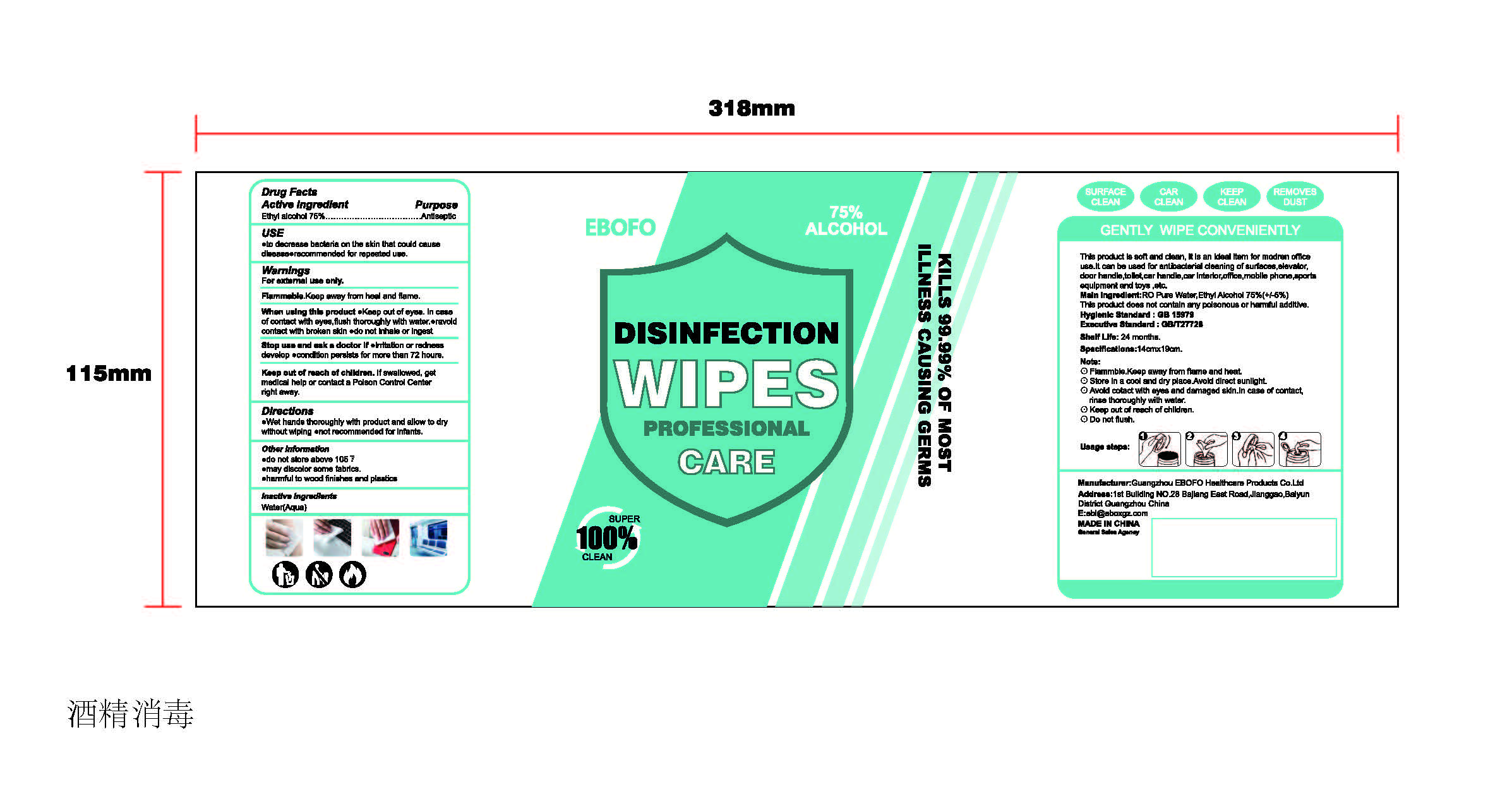 DRUG LABEL: Disinfecting  Wipes
NDC: 81473-002 | Form: CLOTH
Manufacturer: Guangzhou EBOFO Healthcare Products Co.Ltd
Category: otc | Type: HUMAN OTC DRUG LABEL
Date: 20210131

ACTIVE INGREDIENTS: PROPYLENE GLYCOL 0.5 mg/1 mL; BENZALKONIUM CHLORIDE 0.1 mg/1 mL
INACTIVE INGREDIENTS: ETHYLHEXYLGLYCERIN; PHENOXYETHANOL; WATER; GLYCERIN

ACTIVE INGREDIENT

Ethyl alcohol 75%要么 生物杀菌

PURPOSE

Antiseptic

DOSAGE AND ADMINISTRATION

USE: to decrease bacteria on the skin that could cause disease; recommended for repeated use.

WARNINGS

Warnings: For external use only; Flammable. Keep away from heat or flame; When using this product. Keep out of eyes. In case of contact with eyes,flush thoroughly with water.ravoid contact with broken skin .do not inhale or ingest; Stop use and ask a doctor if: irritation or redness develop; condition persists for more than 72 hours; Keep out of reach of children. If swallowed, get medical help or contact a Poison Control Center right away.

Keep out of reach of children. If swallowed, get medical help or contact a Poison Control Center right away.

INACTIVE INGREDIENT

water(Auqa)

INDICATIONS AND USAGE

This product is soft and clean, it is an ideal item for modren office use.It can be used for antibacterial cleaning of surfaces,elevator, door handle.toilet.car handle.car interior,office,mobile phone,sports equipment and toys ,etc.

Other information: do not store above 105F; may discolor some fabrics; harmful to wood finishes and plastics

PACKAGE LABEL

Disinfecting Wipes